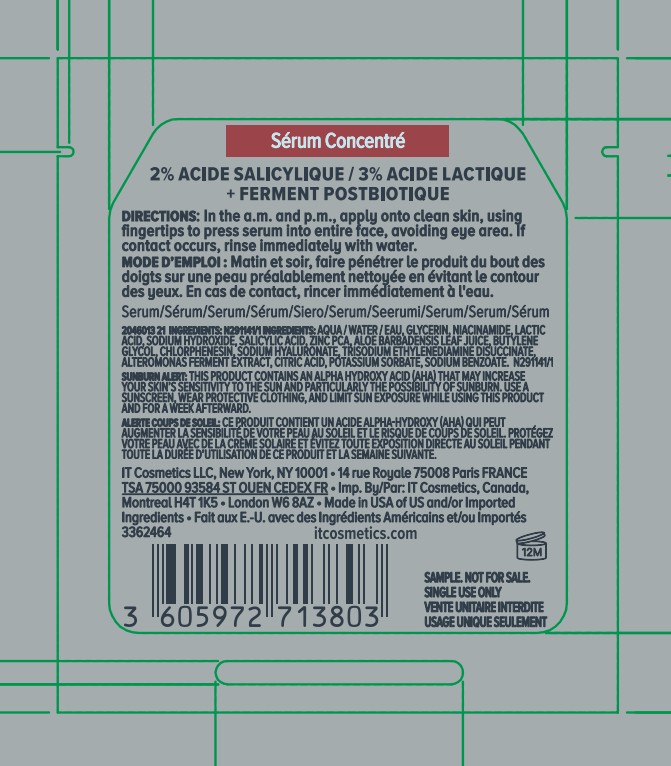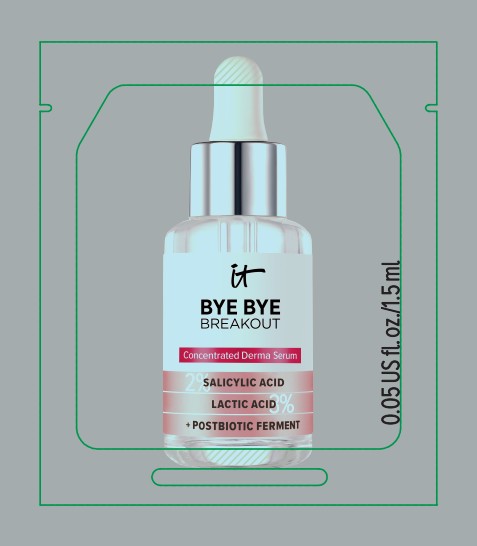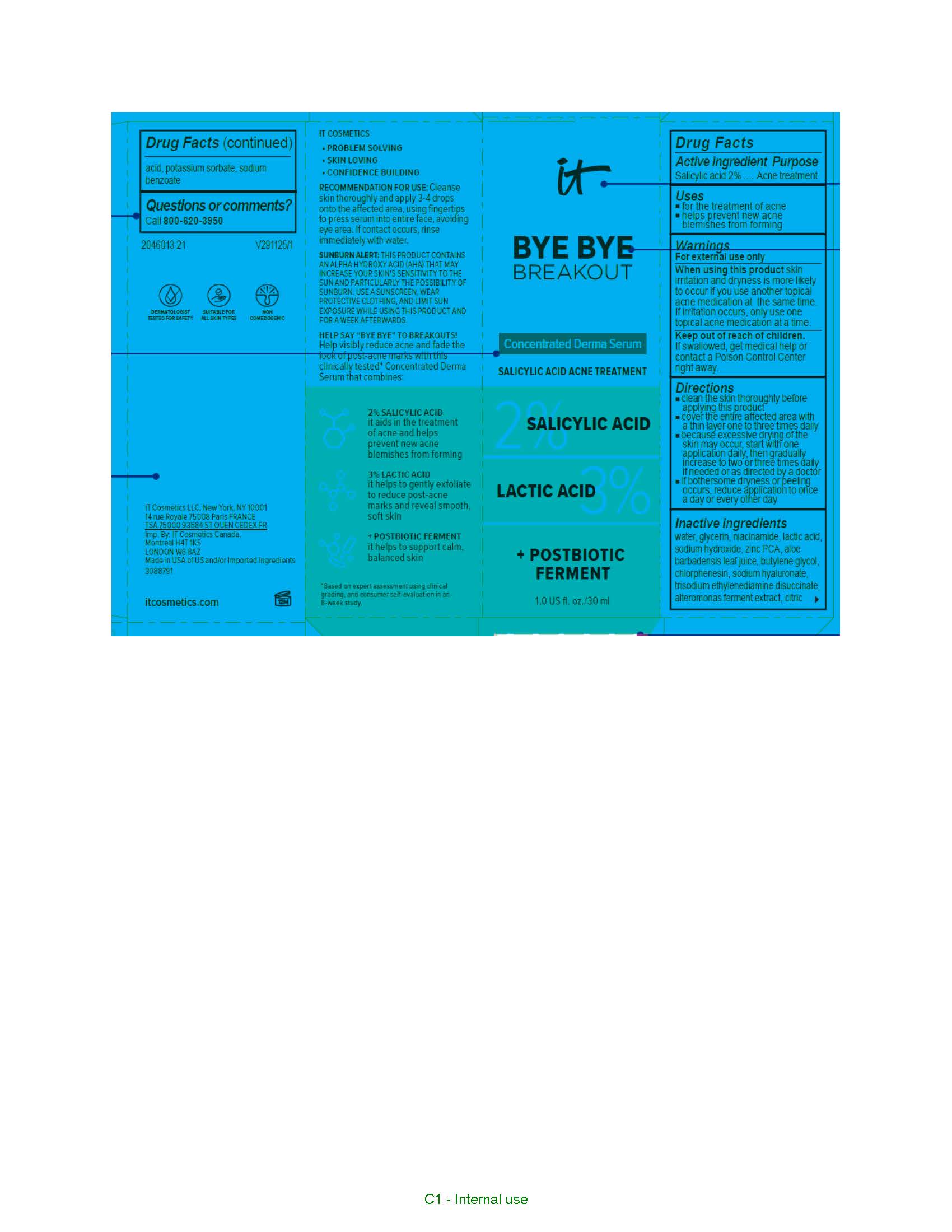 DRUG LABEL: IT Cosmetics Bye Bye Breakout Concentrated Derma Serum Acne Treatment
NDC: 49967-026 | Form: LOTION
Manufacturer: L'Oreal USA Products Inc
Category: otc | Type: HUMAN OTC DRUG LABEL
Date: 20250715

ACTIVE INGREDIENTS: SALICYLIC ACID 20 mg/1 mL
INACTIVE INGREDIENTS: WATER; GLYCERIN; NIACINAMIDE; LACTIC ACID; SODIUM HYDROXIDE; ZINC PIDOLATE; ALOE VERA LEAF; BUTYLENE GLYCOL; CHLORPHENESIN; HYALURONATE SODIUM; TRISODIUM ETHYLENEDIAMINE DISUCCINATE; ALTEROMONAS MACLEODII POLYSACCHARIDES; CITRIC ACID MONOHYDRATE; POTASSIUM SORBATE; SODIUM BENZOATE

Drug Facts

Active ingredient

Salicylic acid 2%

Purpose

Acne treatment

Use

- for the treatment of acne
- helps prevent new acne blemishes from forming

Warnings

For external use only

When using this product

skin irritation and dryness is more likely to occur if you use another topical acne medication at the same time. If irritation occurs, only use one topical acne medication at a time.

Keep out of reach of children.

If swallowed, get medical help or contact a Poison Control Center right away.

Directions

- clean the skin thoroughly before applying this product
- cover the entire affected area with a thin layer one to three times daily
- because excessive drying of the skin may occur, start with one application daily, then gradually ingrease to two or three times dialy if neded or as directed by a doctor
- if bothersome dryness or peeling occurs, reduce application to once a day or every other dayl

Inactive ingredients

water, glycerin, niacinamide, lactic acid, sodium hydroxide, zinc PCA, aloe barbadensis leaf juice, butylene glycol, chlorphenesin, sodium hyaluronate, trisodium ethylenediamine disuccinate, alteromonas ferment extract, citric acid, potassium sorbate, sodium benzoate

Questions or comments?

Call 800-620-3950